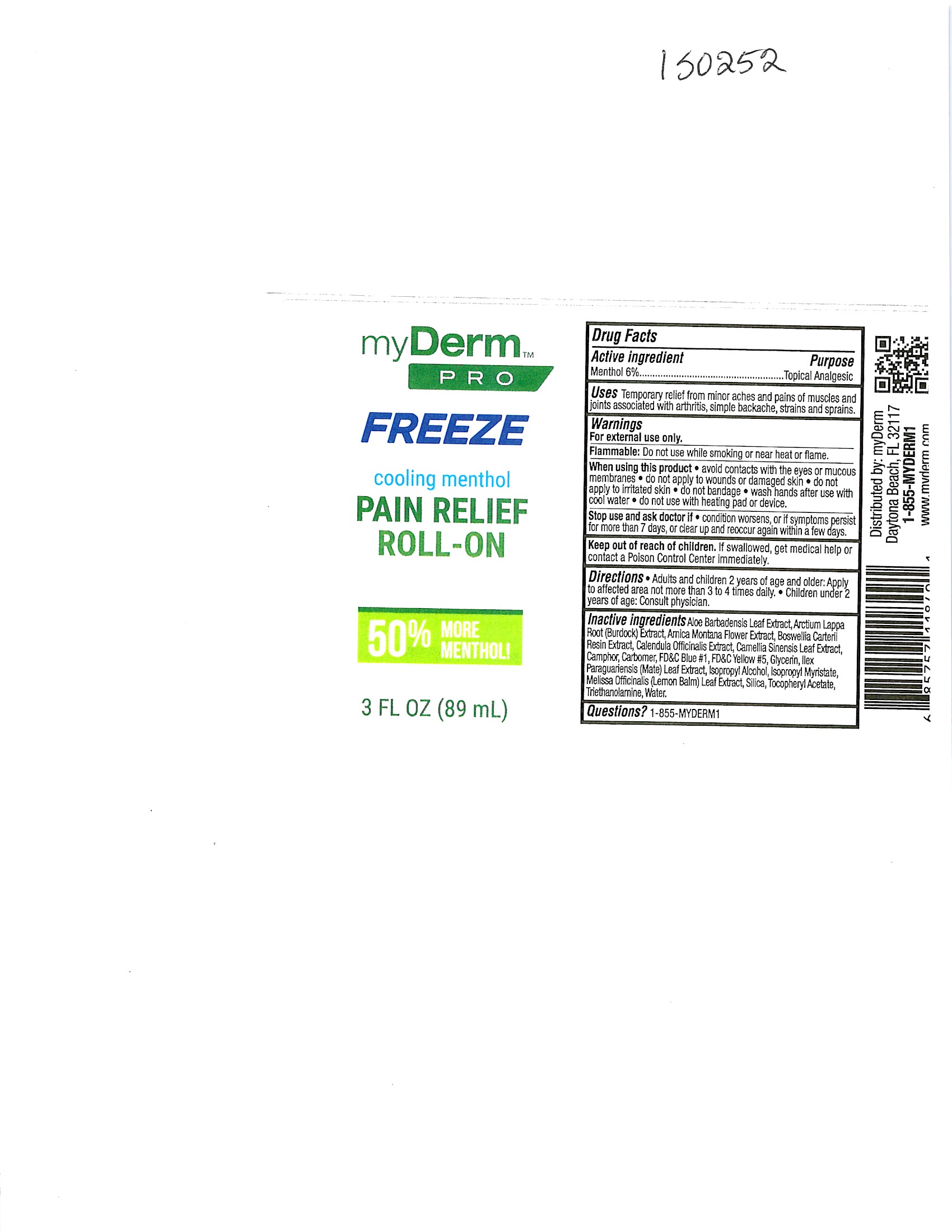 DRUG LABEL: MyDerm Pro Freeze Cooling Menthol Pain Relief Roll-On
NDC: 72667-073 | Form: GEL
Manufacturer: Inspec Solutions
Category: otc | Type: HUMAN OTC DRUG LABEL
Date: 20240624

ACTIVE INGREDIENTS: MENTHOL 6 g/100 g
INACTIVE INGREDIENTS: GREEN TEA LEAF; CAMPHOR, (-)-; CALENDULA OFFICINALIS FLOWER; FRANKINCENSE; FD&C YELLOW NO. 5; ARNICA MONTANA FLOWER; CARBOMER HOMOPOLYMER, UNSPECIFIED TYPE; GLYCERIN; ISOPROPYL ALCOHOL; PHENOXYETHANOL; .ALPHA.-TOCOPHEROL ACETATE; FD&C BLUE NO. 1; ISOPROPYL MYRISTATE; ILEX PARAGUARIENSIS LEAF; MELISSA OFFICINALIS LEAF; SILICON DIOXIDE; TROLAMINE; ALOE VERA LEAF; ARCTIUM LAPPA ROOT

MyDerm Pro Freeze Cooling Menthol Pain Relief Roll-On (IS0252)

Active Ingredient

Menthol 6%

When using this product avoid contacts with the eyes or mucous membranes. do not apply to wounds or damaged skin. do not apply to irritated skin. do not bandage. wash hands after use with cool water. do not use with heating pad or device.

PURPOSE

Menthol 6%------------------------------------------------------------Topical Analgesic

WARNINGS

For external use only.

Stop use and ask doctor if condition worsens, or if symtoms persist for more than 7 days, or clean up and reoccur again within a few days.

keep out of reach of children if swallowed,get medical help or contact a poson Control Center Immediately.

Inactive Ingredient

Aloe Barbadensis Leaf Juice

Arctium Lappa Root Extract

Arnica Montana Flower Extract

Boswellia Carterii resin Extract

Calendula Officinalis Extract

Camellia Sinensis Leaf Extract

Camphor

Carbomer

FD & C Blue #1

FD & C Yellow #5

Glycerin

Isopropyl Alcohol

Isopropyl Myristate

llex Paraguariensis Leaf Extract

Melissa Officinalis Leaf Extract

Phenoxyethanol

Silicon dioxide

Tocopheryl Acetate

Triethanolamine

Water

DOSAGE AND ADMINISTRATION

Direction: Apply to affectered area not more that 3 to 4 times daily.